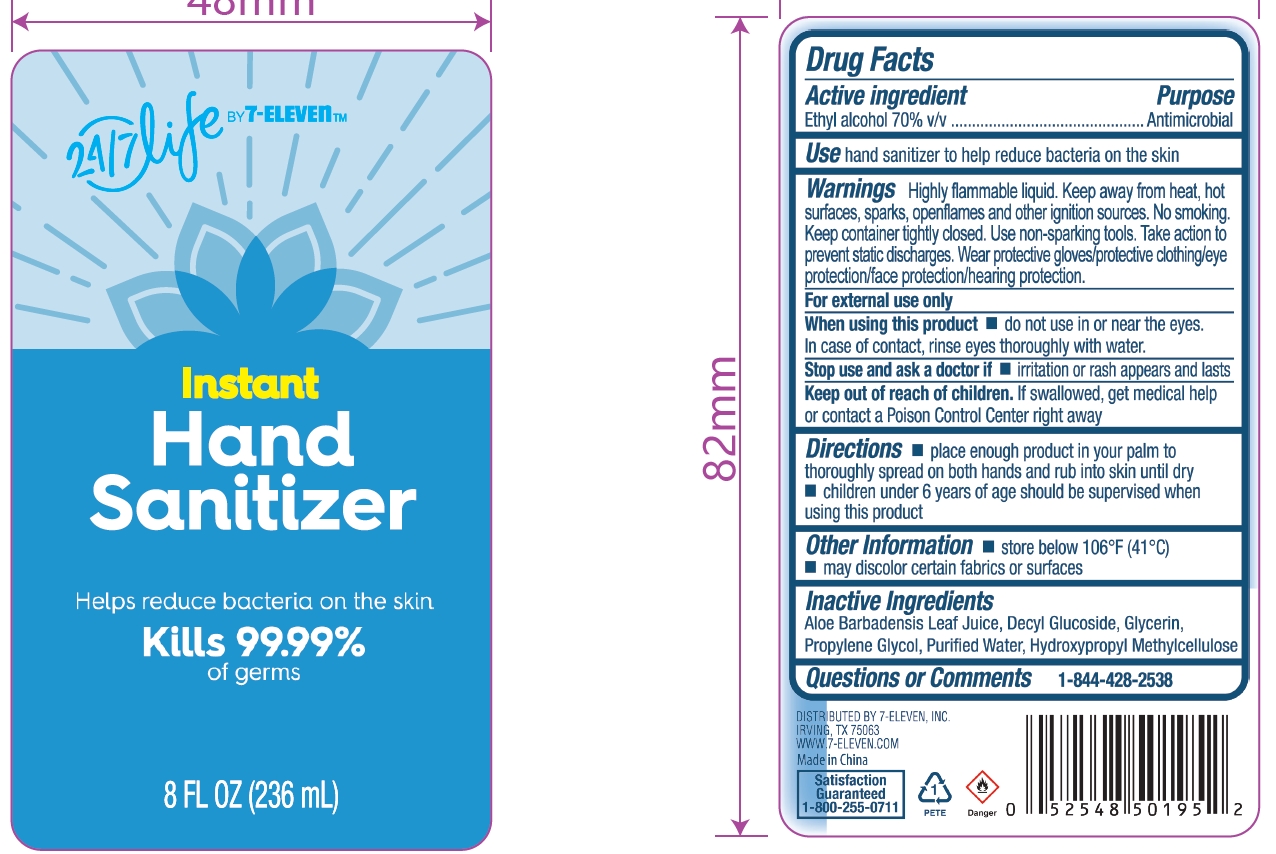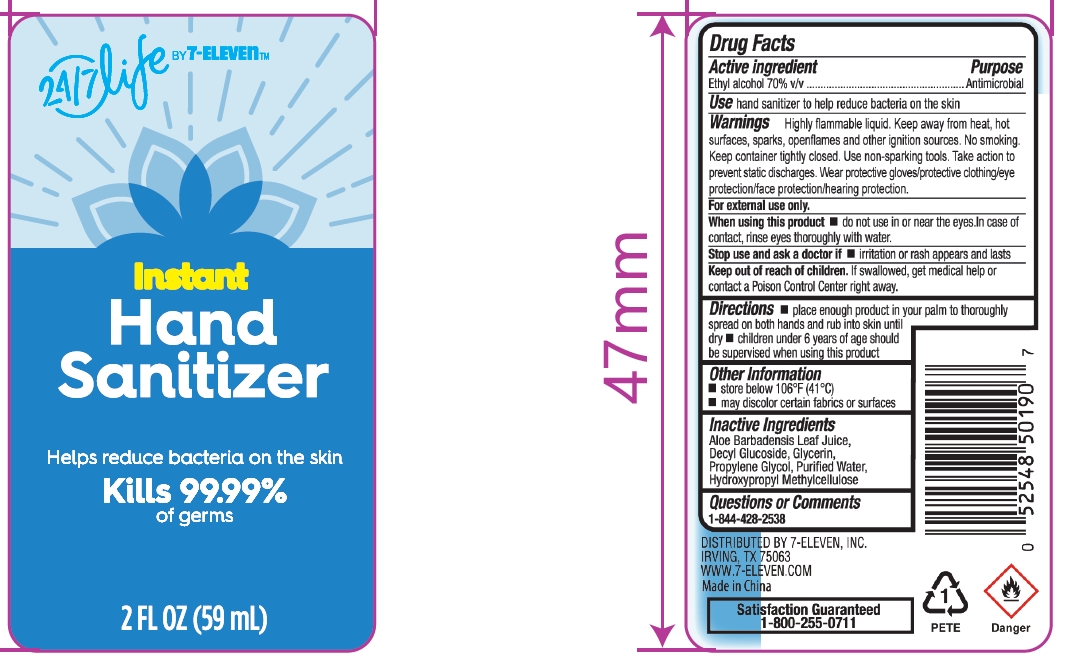 DRUG LABEL: 24 7 life by 7 Eleven
NDC: 10202-400 | Form: GEL
Manufacturer: 7-ELEVEN, INC.
Category: otc | Type: HUMAN OTC DRUG LABEL
Date: 20260210

ACTIVE INGREDIENTS: ALCOHOL 70 mL/100 mL
INACTIVE INGREDIENTS: WATER; HYPROMELLOSE, UNSPECIFIED; ALOE BARBADENSIS LEAF JUICE; DECYL GLUCOSIDE; GLYCERIN; PROPYLENE GLYCOL

10202-400 24 7 life by 7 Eleven Instant Hand Sanitizer

Active ingredient

Ethyl alcohol 70% v/v

Purpose

Antimicrobial

Use

hand sanitizer to help reduce bacteria on the skin

Warnings

Highly flammable liquid. Keep away from heat, hot surfaces, sparks, openflames and other ignition sources. No smoking. Keep container tightly closed. Use non-sparking tools. Take action to prevent static discharges. Wear protective gloves/protective clothing/eye protection/face protection/hearing protection.

For external use only

When using this product

• do not use in or near the eyes. In case of contact, rinse eyes thoroughly with water.

Stop use and ask a doctor if

• irritation or rash appears and lasts

Keep out of reach of children.

If swallowed, get medical help or contact a Poison Control Center right away

Directions

• place enough product in your palm to thoroughly spread on both hands and rub into skin until dry • children under 6 years of age should be supervised when using this product

Other information

• store below 106°F (41°C) • may discolor certain fabrics or surfaces

Inactive ingredients

Aloe Barbadensis Leaf Juice, Decyl Glucoside, Glycerin, Propylene Glycol, Purified Water, Hydroypropyl Methylcellulose

Questions or Comments

1-844-428-2538

PACKAGE LABEL

2 FL OZ（59 mL)
NDC: 10202-400-01

PACKAGE LABEL

8 FL OZ（236 mL)
NDC: 10202-400-02